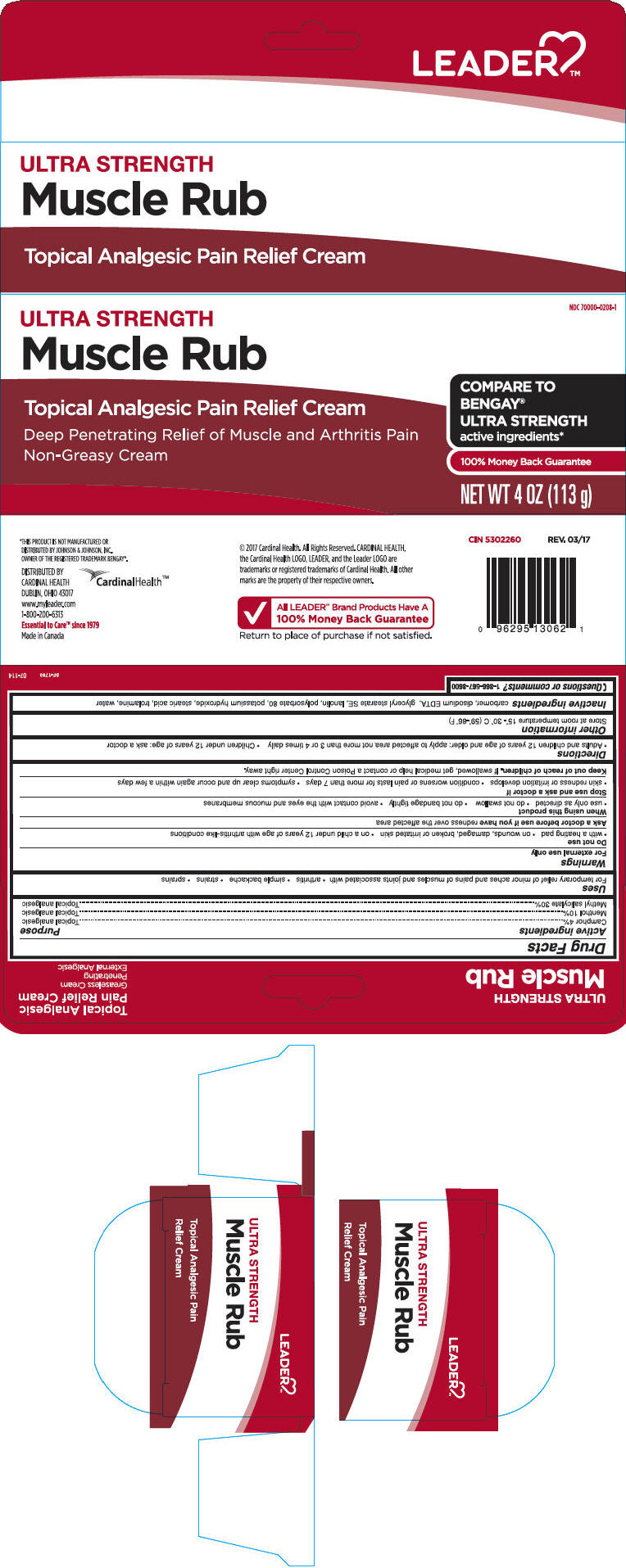 DRUG LABEL: Leader Ultra Strength Muscle Rub
NDC: 70000-0208 | Form: CREAM
Manufacturer: Cardinal Health, 110 dba LEADER
Category: otc | Type: HUMAN OTC DRUG LABEL
Date: 20240209

ACTIVE INGREDIENTS: Camphor (Synthetic) 40 mg/1 g; Menthol, Unspecified Form 100 mg/1 g; Methyl Salicylate 300 mg/1 g
INACTIVE INGREDIENTS: CARBOMER HOMOPOLYMER, UNSPECIFIED TYPE; Edetate Disodium; Glyceryl Stearate SE; Lanolin; Polysorbate 80; Potassium Hydroxide; Stearic Acid; Trolamine; Water

Leader Ultra Strength Muscle Rub
Topical Analgesic

ACTIVE INGREDIENT

Active ingredients | Purpose
Camphor 4% | Topical Analgesic
Menthol 10.0% | Topical Analgesic
Methyl Salicylate 30% | Topical Analgesic

Uses

for the temporary relief of minor aches and muscles and joints associated with:

- arthritis
- simple backache
- strains
- sprains

Warnings

For external use only

Do not use

- with a heating pad
- on wounds, damaged, broken or irritated skin
- on a child under 12 years of age with arthritis-like conditions

Ask a doctor before use if you have redness over the affected area

When using this product

- use only as directed
- do not swallow
- do not bandage tightly
- avoid contact with the eyes and mucous membranes

Stop use and consult a doctor if

- skin redness or irritation develops
- condition worsens or pain lasts for more than 7 days
- symptoms clear up and occur again within a few days

Keep out of reach of children. If swallowed, get medical help or contact a Poison Control Center right away.

Directions

- Adults and children 12 years of age and older: apply to affected area not more than 3 or 4 times daily
- children under 12 years of age: ask a doctor

Other information

Store at room temperature 15° - 30° C (59° - 86° F)

Inactive ingredients

Carbomer, Disodium EDTA, Glyceryl Stearate SE, Lanolin, Polysorbate 80, Potassium Hydroxide, Stearic Acid, Trolamine, Water.

Questions or comments?

1-866-567-8600

DISTRIBUTED BY
CARDINAL HEALTH
DUBLIN, OHIO 43017

PRINCIPAL DISPLAY PANEL - 113 g Tube Carton

NDC 70000-0208-1

ULTRA STRENGTH
Muscle Rub

Topical Analgesic Pain Relief Cream

Deep Penetrating Relief of Muscle and Arthritis Pain
Non-Greasy Cream

COMPARE TO
BENGAY®
ULTRA STRENGTH
active ingredients*

100% Money Back Guarantee

NET WT 4 OZ (113 g)